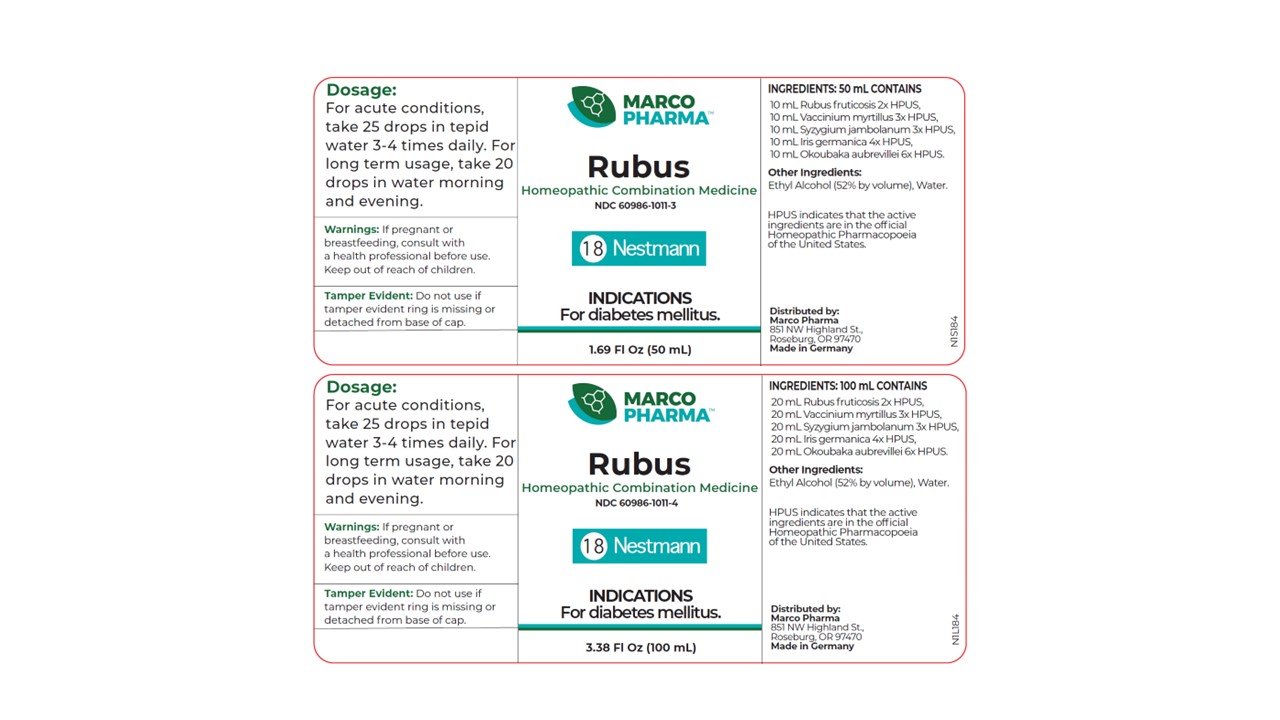 DRUG LABEL: Rubus
NDC: 60986-1011 | Form: LIQUID
Manufacturer: Marco Pharma International LLC.
Category: homeopathic | Type: HUMAN OTC DRUG LABEL
Date: 20260112

ACTIVE INGREDIENTS: BLACKBERRY 2 [hp_X]/100 mL; IRIS X GERMANICA ROOT 4 [hp_X]/100 mL; BILBERRY 3 [hp_X]/100 mL; SYZYGIUM CUMINI SEED 3 [hp_X]/100 mL; OKOUBAKA AUBREVILLEI BARK 6 [hp_X]/100 mL
INACTIVE INGREDIENTS: ALCOHOL; WATER

Drug Facts

Active Ingredients

Rubus Fruticosus 2xHPUS

Iris Germanica 4xHPUS

Vaccinium Myrtillus 3xHPUS

Syzygium Jambolanum 3xHPUS

Okoubaka Aubrevillei 6xHPUS

The letters HPUS indicates that the components in this product are officially monographed in the Homeopathic Pharmacopoeia of United Sates.

Purpose

For temporary relief of pancreatic discomforts.

Keep out of reach of children.

Suggested use

Dosage: For acute conditions take 25 drops in water 3-4 times daily. For long-term usage, take 20 drops in water morning and evening.

RECENT MAJOR CHANGES

Dosage: For acute conditions take 25 drops in water 3-4 times daily. For long-term usage, take 20 drops in water morning and evening.

Warnings

If pregnant or breast-feeding, consult a health professional before use. In case of accidental overdose, seek professional assistance or contact a poison control center immediately.

DOSAGE AND ADMINISTRATION

(Read Suggested Use Section)

Inactive Ingredients

Ethyl alcohol (52% by vol.) and Water